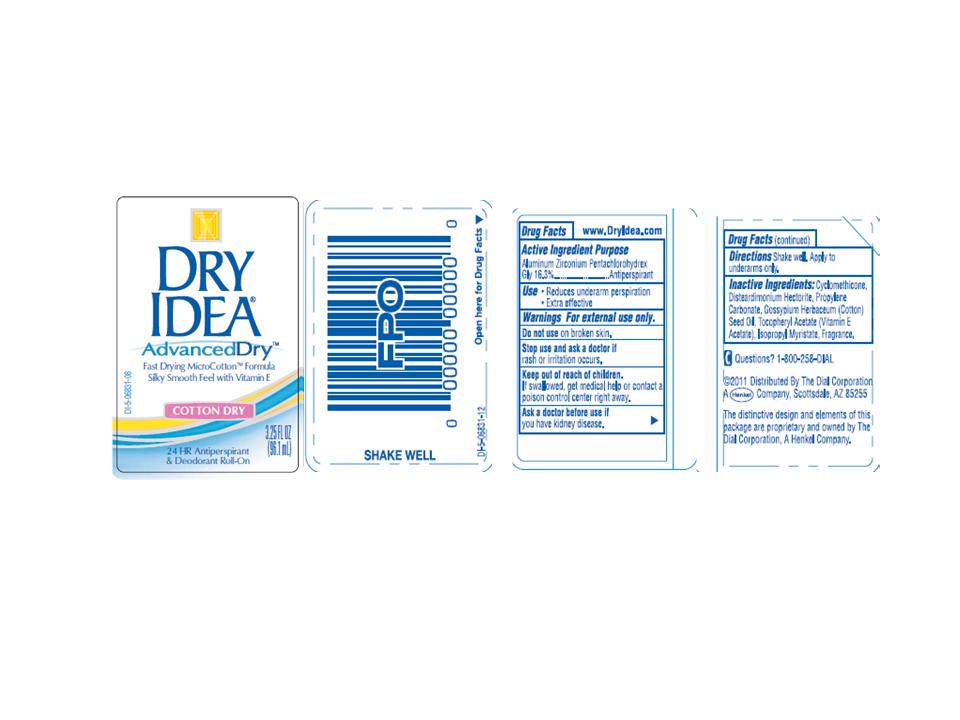 DRUG LABEL: Dry Idea Advanced Dry-Cotton Dry
NDC: 54340-006 | Form: LIQUID
Manufacturer: The Dial Corporation
Category: otc | Type: HUMAN OTC DRUG LABEL
Date: 20111118

ACTIVE INGREDIENTS: Aluminum Zirconium Pentachlorohydrex  gly 16.3 g/100 mL
INACTIVE INGREDIENTS: Cyclomethicone 74.5 g/100 mL; Propylene Carbonate 1 g/100 mL; .ALPHA.-TOCOPHEROL ACETATE, D- 0.1 g/100 mL; STEARYL MYRISTATE 0.1 g/100 mL; Bentonite 4.1 g/100 mL

Drug Facts

Active Ingredient Purpose

Aluminum Zirconium Pentacholrohydrex Gly 16.3%.......Antiperspirant

PURPOSE

Antiperspirant

Use

- Reduces underarm perspiration
- Extra effective

Warnings for external use only.

Do not use on broken skin.

Stop use and ask a doctor if

rash or irritation occurs.

Keep out of reach of children.

If swallowed, get medical help or contact a poison control center right away.

Ask a doctor before use if

you have kidney disease.

DOSAGE AND ADMINISTRATION

Directions Shake well. Apply to underarms only.

INACTIVE INGREDIENT

Inactive Ingredients: Cyclomethicone, Disteardimonium Hectorite, Propylene Carbonate, Gossypium Herbaceum(Cotton) Seed oil,Tocopheryl Acetate (Vitamin E Acetate),Isopropyl Myristate, Fragrance,Zea Mays(Corn) Starch.

Questions? 1-800-258-DIAL

PACKAGE LABEL

dryidea-cotton